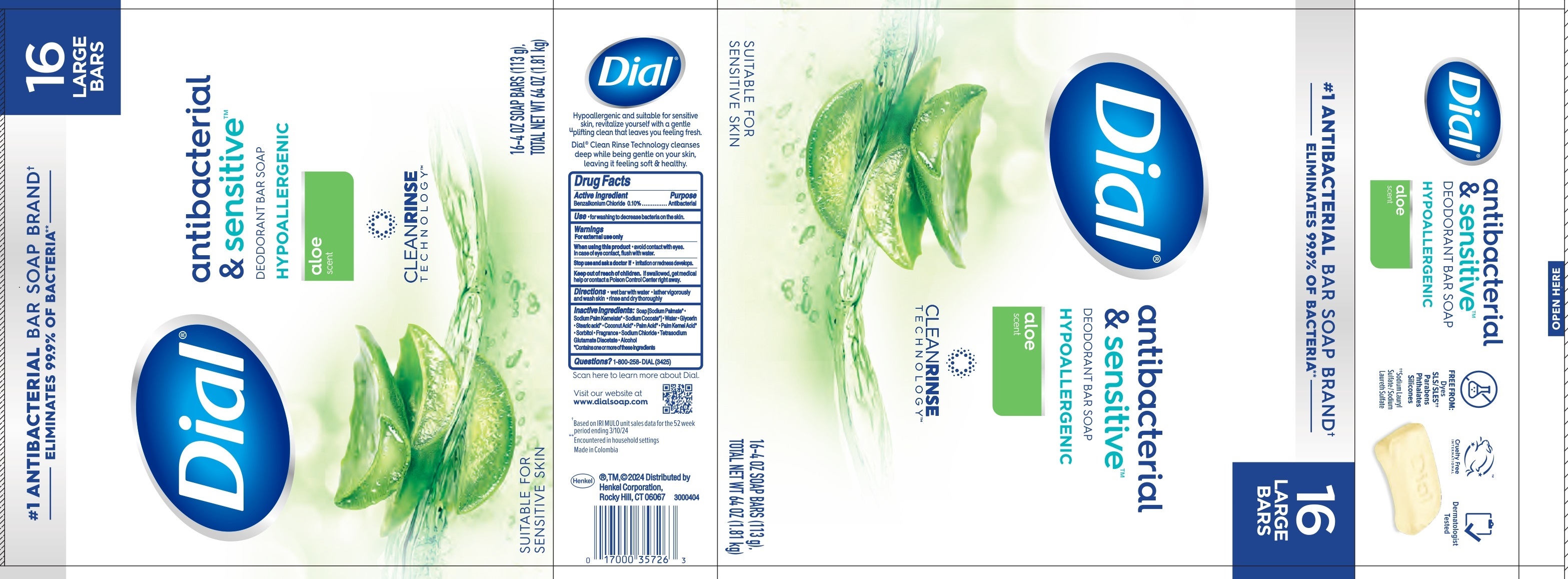 DRUG LABEL: Dial antibacterial and sensitive hypoallergenic bar
NDC: 54340-283 | Form: SOAP
Manufacturer: Henkel Corporation
Category: otc | Type: HUMAN OTC DRUG LABEL
Date: 20240918

ACTIVE INGREDIENTS: BENZALKONIUM CHLORIDE 0.1 g/100 g
INACTIVE INGREDIENTS: SODIUM PALMATE; PALM ACID; SORBITOL; SODIUM COCOATE; PALM KERNEL ACID; SODIUM CHLORIDE; GLYCERIN; STEARIC ACID; COCONUT ACID; TETRASODIUM GLUTAMATE DIACETATE; ALCOHOL; SODIUM PALM KERNELATE; WATER

Dial antibacterial & sensitive Hypoallergenic bar aloe scent

Active ingredient

Benzalkonium Chloride 0.10%

Purpose

Antibacterial

INDICATIONS AND USAGE

Use • for washing to decrease bacteria on the skin.

Warnings

For external use only

When using this product • avoid contact with eyes. In case of eye contact, flush with water.

Stop use and ask a doctor if • irritation or redness develops.

Keep out of reach of children. If swallowed, get medical help or contact a Poison Control Center right away.

DOSAGE AND ADMINISTRATION

Directions • wet bar with water • lather vigorously and wash skin • rinse and dry thoroughly

INACTIVE INGREDIENT

Inactive ingredients: Soap [Sodium Palmate* • Sodium Palm Kernelate* • Sodium Cocoate*] • Water • Glycerin • Stearic Acid* • Coconu Acid* • Palm Acid* • Palm Kernel Acid* • Sorbitol • Frgrance • Sodium Chloride • Tetrasodium Glutamate Diacetate • Alcohol

*Contains one or more of these ingredients

Questions? 1-800-258-DIAL (3425)

Henkel ® TM, ©2024 Distributed by

Henkel Corporation,

Rocky Hill, CT 06067

PACKAGE LABEL

Dial® antibacterial & sensitive™

DEODORANT BAR SOAP

HYPOALLERGENIC

aloe scent

CLEAN RINSE

TECHNOLOGY™

SUITABLE FOR SENSITIVE SKIN

16-4 OZ SOAP BARS (113g),

TOTAL NET WT 64 OZ (1.81 kg)

16 LARGE BARS